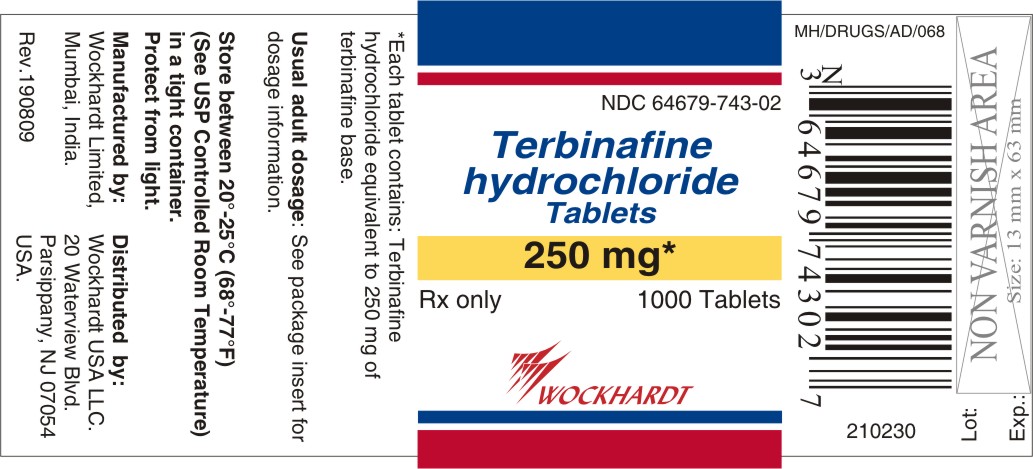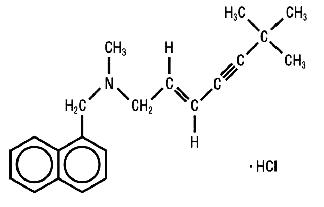 DRUG LABEL: TERBINAFINE HYDROCHLORIDE
NDC: 55648-743 | Form: TABLET
Manufacturer: Wockhardt Limited
Category: prescription | Type: HUMAN PRESCRIPTION DRUG LABEL
Date: 20120907

ACTIVE INGREDIENTS: TERBINAFINE HYDROCHLORIDE 250 mg/1 1
INACTIVE INGREDIENTS: CELLULOSE, MICROCRYSTALLINE; MAGNESIUM STEARATE; SILICON DIOXIDE; SODIUM STARCH GLYCOLATE TYPE A POTATO; HYPROMELLOSE 2910 (6 MPA.S)

Terbinafine Hydrochloride Tablets

Rx only

Prescribing Information

DESCRIPTION

Terbinafine hydrochloride tablets contain the synthetic allylamine antifungal compound terbinafine hydrochloride.

Chemically, terbinafine hydrochloride is (E)-N-(6,6-dimethyl-2-hepten-4-ynyl)-N-methyl-1-naphthalenemethanamine hydrochloride. The empirical formula C21H26ClN with a molecular weight of 327.90, and the following structural formula:

Terbinafine hydrochloride is a white to off-white crystalline powder. It is freely soluble in methanol and methylene chloride, soluble in ethanol, and slightly soluble in water.

Each tablet contains:

Active Ingredients: terbinafine hydrochloride (equivalent to 250 mg base)

Inactive Ingredients: microcrystalline cellulose, NF; hypromellose 6 cps, USP; sodium starch glycolate, NF; colloidal silicon dioxide, NF; magnesium stearate, NF

CLINICAL PHARMACOLOGY

Pharmacokinetics

Following oral administration, terbinafine is well absorbed (>70%) and the bioavailability of terbinafine hydrochloride tablets as a result of first-pass metabolism is approximately 40%. Peak plasma concentrations of 1 µg/mL appear within 2 h after a single 250 mg dose; the AUC (area under the curve) is approximately 4.56 µg·h/mL. An increase in the AUC of terbinafine of less than 20% is observed when terbinafine hydrochloride tablets is administered with food. No clinically relevant age-dependent changes in steady-state plasma concentrations of terbinafine have been reported. In patients with renal impairment (creatinine clearance ≤50mL/min) or hepatic cirrhosis, the clearance of terbinafine is decreased by approximately 50% compared to normal volunteers. No effect of gender on the blood levels of terbinafine was detected in clinical trials. In plasma, terbinafine is >99% bound to plasma proteins and there are no specific binding sites. At steady-state, in comparison to a single dose, the peak concentration of terbinafine is 25% higher and plasma AUC increases by a factor of 2.5; the increase in plasma AUC is consistent with an effective half-life of ~36 hours. Terbinafine is distributed to the sebum and skin. A terminal half-life of 200-400 h may represent the slow elimination of terbinafine from tissues such as skin and adipose. Prior to excretion, terbinafine is extensively metabolized. No metabolites have been identified that have antifungal activity similar to terbinafine. Approximately 70% of the administered dose is eliminated in the urine.

Microbiology

Terbinafine hydrochloride is a synthetic allylamine derivative. Terbinafine hydrochloride is hypothesized to act by inhibiting squalene epoxidase, thus blocking the biosynthesis of ergosterol, an essential component of fungal cell membranes. In vitro, mammalian squalene epoxidase is only inhibited at higher (4000 fold) concentrations than is needed for inhibition of the dermatophyte enzyme. Depending on the concentration of the drug and the fungal species test in vitro, terbinafine hydrochloride may be fungicidal. However, the clinical significance of in vitro data is unknown.

Terbinafine has been shown to be active against most strains of the following microorganisms both in vitro and in clinical infections as described in the INDICATIONS AND USAGE section:

Trichophyton mentagrophytes

Trichophyton rubrum

The following in vitro data are available, but their clinical significance is unknown. In vitro, terbinafine exhibits satisfactory MIC's against most strains of the following microorganisms; however, the safety and efficacy of terbinafine in treating clinical infections due to these microorganisms have not been established in adequate and well-controlled clinical trials:

Candida albicans

Epidermophyton floccosum

Scopulariopsis brevicaulis

CLINICAL STUDIES

The efficacy of terbinafine hydrochloride tablets in the treatment of onychomycosis is illustrated by the response of patients with toenail and/or fingernail infections who participated in three US/Canadian placebo-controlled clinical trials.

Results of the first toenail study, as assessed at week 48 (12 weeks of treatment with 36 weeks follow-up after completion of therapy), demonstrated mycological cure, defined as simultaneous occurrence of negative KOH plus negative culture, in 70% of patients. Fifty-nine percent (59%) of patients experienced effective treatment (mycological cure plus 0% nail involvement or >5mm of new unaffected nail growth); 38% of patients demonstrated mycological cure plus clinical cure (0% nail involvement).

In a second toenail study of dermatophytic onychomycosis, in which non-dermatophytes were also cultured, similar efficacy against the dermatophytes was demonstrated. The pathogenic role of the non-dermatophytes cultured in the presence of dermatophytic onychomycosis has not been established. The clinical significance of this association is unknown.

Results of the fingernail study, as assessed at week 24 (6 weeks of treatment with 18 weeks follow-up after completion of therapy), demonstrated mycological cure in 79% of patients, effective treatment in 75% of the patients, and mycological cure plus clinical cure in 59% of the patients.

The mean time to overall success was approximately 10 months for the first toenail study and 4 months for the fingernail study. In the first toenail study, for patients evaluated at least six months after achieving clinical cure and at least one year after completing terbinafine hydrochloride tablets therapy, the clinical relapse rate was approximately 15%.

INDICATIONS AND USAGE

Terbinafine hydrochloride tablets are indicated for the treatment of onychomycosis of the toenail or fingernail due to dermatophytes (tinea unguium) (see DOSAGE AND ADMINISTRATION and CLINICAL STUDIES).

Prior to initiating treatment, appropriate nail specimens for laboratory testing (KOH preparation, fungal culture, or nail biopsy) should be obtained to confirm the diagnosis of onychomycosis.

CONTRAINDICATIONS

Terbinafine hydrochloride tablets are contraindicated in individuals with hypersensitivity to terbinafine or to any other ingredients of the formulation.

WARNINGS

Rare cases of liver failure, some leading to death or liver transplant, have occurred with the use of terbinafine hydrochloride tablets for the treatment of onychomycosis in individuals with and without pre-existing liver disease.

In the majority of liver cases reported in association with terbinafine hydrochloride tablets use, the patients had serious underlying systemic conditions and an uncertain causal association with terbinafine hydrochloride tablets. The severity of hepatic events and/or their outcome may be worse in patients with active or chronic liver disease (see PRECAUTIONS). Treatment with terbinafine hydrochloride tablets should be discontinued if biochemical or clinical evidence of liver injury develops (see PRECAUTIONS below).

There have been isolated reports of serious skin reactions (e.g., Stevens-Johnson Syndrome and toxic epidermal necrolysis). If progressive skin rash occurs, treatment with terbinafine hydrochloride tablets should be discontinued.

PRECAUTIONS

General

Terbinafine hydrochloride tablets are not recommended for patients with chronic or active liver disease. Before prescribing terbinafine hydrochloride tablets, pre-existing liver disease should be assessed. Hepatotoxicity may occur in patients with and without pre-existing liver disease. Pretreatment serum transaminase (ALT and AST) tests are advised for all patients before taking terbinafine hydrochloride tablets. Patients prescribed terbinafine hydrochloride tablets should be warned to report immediately to their physician any symptoms of persistent nausea, anorexia, fatigue, vomiting, right upper abdominal pain or jaundice, dark urine or pale stools (see WARNINGS). Patients with these symptoms should discontinue taking oral terbinafine, and the patient's liver function should be immediately evaluated.

In patients with renal impairment (creatinine clearance ≤50 mL/ min), the use of terbinafine hydrochloride tablets has not been adequately studied, and therefore, is not recommended (see CLINICAL PHARMACOLOGY, Pharmacokinetics).

During postmarketing experience, precipitation and exacerbation of cutaneous and systemic lupus erythematosus have been reported infrequently in patients taking terbinafine hydrochloride tablets. Terbinafine hydrochloride tablets therapy should be discontinued in patients with clinical signs and symptoms suggestive of lupus erythematosus.

Changes in the ocular lens and retina have been reported following the use of terbinafine hydrochloride tablets in controlled trials. The clinical significance of these changes is unknown.

Transient decreases in absolute lymphocyte counts (ALC) have been observed in controlled clinical trials. In placebo-controlled trials, 8/465 terbinafine hydrochloride tablets-treated patients (1.7%) and 3/137 placebo-treated patients (2.2%) had decreases in ALC to below 1000/mm^3 on two or more occasions. The clinical significance of this observation is unknown. However, in patients with known or suspected immunodeficiency, physicians should consider monitoring complete blood counts in individuals using terbinafine hydrochloride tablets therapy for greater than six weeks.

Isolated cases of severe neutropenia have been reported. These were reversible upon discontinuation of terbinafine hydrochloride tablets, with or without supportive therapy. If clinical signs and symptoms suggestive of secondary infection occur, a complete blood count should be obtained. If the neutrophil count is ≤1,000 cells/mm^3, terbinafine hydrochloride tablets should be discontinued and supportive management started.

Drug Interactions

In vivo studies have shown that terbinafine is an inhibitor of the CYP450 2D6 isozyme.

Drugs predominantly metabolized by the CYP450 2D6 isozyme include the following drug classes: tricyclic antidepressants, selective serotonin reuptake inhibitors, beta-blockers, antiarrhythmics class 1C (e.g., flecainide and propafenone) and monoamine oxidase inhibitors Type B. Coadministration of terbinafine hydrochloride tablets should be done with careful monitoring and may require a reduction in dose of the 2D6-metabolized drug. In a study to assess the effects of terbinafine on desipramine in healthy volunteers characterized as normal metabolizers, the administration of terbinafine resulted in a 2-fold increase in Cmax and a 5-fold increase in AUC. In this study, these effects were shown to persist at the last observation at 4 weeks after discontinuation of terbinafine hydrochloride tablets.

In vitro studies with human liver microsomes showed that terbinafine does not inhibit the metabolism of tolbutamide, ethinylestradiol, ethoxycoumarin, and cyclosporine.

In vivo drug-drug interaction studies conducted in healthy volunteer subjects showed that terbinafine does not affect the clearance of antipyrine or digoxin. Terbinafine decreases the clearance of caffeine by 19%. Terbinafine increases the clearance of cyclosporine by 15%.

There have been spontaneous reports of increase or decrease in prothrombin times in patients concomitantly taking oral terbinafine and warfarin, however, a causal relationship between terbinafine hydrochloride tablets and these changes has not been established.

Terbinafine clearance is increased 100% by rifampin, a CYP450 enzyme inducer, and decreased 33% by cimetidine, a CYP450 enzyme inhibitor. Terbinafine clearance is unaffected by cyclosporine.

There is no information available from adequate drug-drug interaction studies with the following classes of drugs: oral contraceptives, hormone replacement therapies, hypoglycemics, theophyllines, phenytoins, thiazide diuretics, and calcium channel blockers.

Carcinogenesis, Mutagenesis, Impairment of Fertility

In a 28-month oral carcinogenicity study in rats, an increase in the incidence of liver tumors was observed in males at the highest dose tested, 69 mg/kg/day [2x the Maximum Recommended Human Dose (MRHD) based on AUC comparisons of the parent terbinafine]; however, even though dose-limiting toxicity was not achieved at the highest tested dose, higher doses were not tested.

The results of a variety of in vitro (mutations in E. coli and S. typhimurium, DNA repair in rat hepatocytes, mutagenicity in Chinese hamster fibroblasts, chromosome aberration and sister chromatid exchanges in Chinese hamster lung cells), and in vivo (chromosome aberration in Chinese hamsters, micronucleus test in mice) genotoxicity tests gave no evidence of a mutagenic or clastogenic potential. Oral reproduction studies in rats at doses up to 300 mg/kg/day (approximately 12x the MRHD based on body surface area comparisons, BSA) did not reveal any specific effects on fertility or other reproductive parameters. Intravaginal application of terbinafine hydrochloride at 150 mg/day in pregnant rabbits did not increase the incidence of abortions or premature deliveries nor affect fetal parameters.

Pregnancy

Pregnancy Category B: Oral reproduction studies have been performed in rabbits and rats at doses up to 300 mg/kg/day (12x to 23x the MRHD, in rabbits and rats, respectively, based on BSA) and have revealed no evidence of impaired fertility or harm to the fetus due to terbinafine. There are, however, no adequate and well-controlled studies in pregnant women. Because animal reproduction studies are not always predictive of human response, and because treatment of onychomycosis can be postponed until after pregnancy is completed, it is recommended that terbinafine hydrochloride tablets not be initiated during pregnancy.

Nursing Mothers

After oral administration, terbinafine is present in breast milk of nursing mothers. The ratio of terbinafine in milk to plasma is 7:1. Treatment with terbinafine hydrochloride tablets is not recommended in nursing mothers.

Pediatric Use

The safety and efficacy of terbinafine hydrochloride tablets have not been established in pediatric patients.

ADVERSE REACTIONS

The most frequently reported adverse events observed in the three US/Canadian placebo-controlled trials are listed in the table below. The adverse events reported encompass gastrointestinal symptoms (including diarrhea, dyspepsia, and abdominal pain), liver test abnormalities, rashes, urticaria, pruritus, and taste disturbances. In general, the adverse events were mild, transient, and did not lead to discontinuation from study participation.

 | Adverse Event |  | Discontinuation
 | Terbinafine Hydrochloride Tablets (%) n= 465 | Placebo (%) n= 137 | Terbinafine Hydrochloride Tablets (%) n=465 | Placebo (%) n= 137
Headache | 12.9 | 9.5 | 0.2 | 0.0
Gastrointestinal Symptoms:
Diarrhea | 5.6 | 2.9 | 0.6 | 0.0
Dyspepsia | 4.3 | 2.9 | 0.4 | 0.0
Abdominal Pain | 2.4 | 1.5 | 0.4 | 0.0
Nausea | 2.6 | 2.9 | 0.2 | 0.0
Flatulence | 2.2 | 2.2 | 0.0 | 0.0
Dermatological Symptoms:
Rash | 5.6 | 2.2 | 0.9 | 0.7
Pruritus | 2.8 | 1.5 | 0.2 | 0.0
Urticaria | 1.1 | 0.0 | 0.0 | 0.0
Liver Enzyme
Abnormalities* | 3.3 | 1.4 | 0.2 | 0.0
Taste Disturbance | 2.8 | 0.7 | 0.2 | 0.0
Visual Disturbance | 1.1 | 1.5 | 0.9 | 0.0
* Liver enzyme abnormalities ≥2x the upper limit of the normal range.

Adverse events, based on worldwide experience with terbinafine hydrochloride tablets use, include: idiosyncratic and symptomatic hepatic injury and more rarely, cases of liver failure, some leading to death or liver transplant, (see WARNINGS and PRECAUTIONS), serious skin reactions (see WARNINGS), severe neutropenia (see PRECAUTIONS), thrombocytopenia, angioedema and allergic reactions (including anaphylaxis). Psoriasiform eruptions or exacerbation of psoriasis, acute generalized exanthematous pustulosis and precipitation and exacerbation of cutaneous and systemic lupus erythematosus have been reported in patients taking terbinafine hydrochloride tablets. Terbinafine hydrochloride tablets may cause taste disturbance (including taste loss) which usually recovers within several weeks after discontinuation of the drug. There have been reports of prolonged (greater than one year) taste disturbance. Taste disturbances associated with oral terbinafine have been reported to be severe enough to result in decreased food intake leading to significant and unwanted weight loss.

Other adverse reactions which have been reported include malaise, fatigue, vomiting, arthralgia, myalgia, and hair loss.

Clinical adverse effects reported spontaneously since the drug was marketed include altered prothrombin time (prolongation and reduction) in patients concomitantly treated with warfarin and terbinafine hydrochloride tablets and agranulocytosis (rare).

OVERDOSAGE

Clinical experience regarding overdose with terbinafine hydrochloride tablets is limited. Doses up to 5 grams (20 times the therapeutic daily dose) have been taken without inducing serious adverse reactions. The symptoms of overdose included nausea, vomiting, abdominal pain, dizziness, rash, frequent urination, and headache.

DOSAGE AND ADMINISTRATION

Terbinafine hydrochloride tablets, one 250 mg tablet, should be taken once daily for 6 weeks by patients with fingernail onychomycosis. Terbinafine hydrochloride tablets, one 250 mg tablet, should be taken once daily for 12 weeks by patients with toenail onychomycosis. The optimal clinical effect is seen some months after mycological cure and cessation of treatment. This is related to the period required for outgrowth of healthy nail.

HOW SUPPLIED

Terbinafine hydrochloride tablets 250 mg, supplied as white circular, bi-convex, bevelled tablets embossed with ‘W’ on one side and ‘743’ on other side.

Bottles of 30 tablets................................NDC 64679-743-01

Bottles of 1000 tablets............................NDC 64679-743-02

Bottles of 100 tablets..............................NDC 64679-743-03

Cartons of 1 blister card (30 tablets) ......NDC 64679-743-05

Store at 20° - 25 °C (68° - 77 ° F); in a tight container. Protect from light.

ANIMAL TOXICOLOGY

A wide range of in vivo studies in mice, rats, dogs, and monkeys, and in vitro studies using rat, monkey, and human hepatocytes suggest that peroxisome proliferation in the liver is a rat-specific finding. However, other effects, including increased liver weights and APTT, occurred in dogs and monkeys at doses giving Css trough levels of the parent terbinafine 2-3x those seen in humans at the MRHD. Higher doses were not tested.

Manufactured by:

Wockhardt Limited,

Mumbai, India.

Distributed by:

Wockhardt USA LLC.

20 Waterview Blvd.

Parsippany, NJ 07054

USA.

Rev.190809